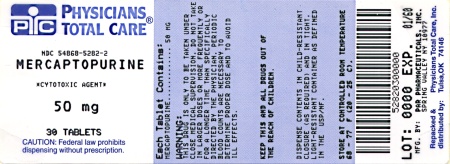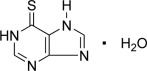 DRUG LABEL: mercaptopurine
NDC: 54868-5282 | Form: TABLET
Manufacturer: Physicians Total Care, Inc.
Category: prescription | Type: HUMAN PRESCRIPTION DRUG LABEL
Date: 20121001

ACTIVE INGREDIENTS: mercaptopurine 50 mg/1 1
INACTIVE INGREDIENTS: cellulose, microcrystalline; lactose; stearic acid; silicon dioxide

MERCAPTOPURINE TABLETS USP, 50 MG
Rx only

CAUTION

Mercaptopurine is a potent drug. It should not be used unless a diagnosis of acute lymphatic leukemia has been adequately established and the responsible physician is experienced with the risks of mercatopurine and knowledgeable in assessing response to chemotherapy.

DESCRIPTION

Mercaptopurine was synthesized and developed by Hitchings, Elion, and associates at the Wellcome Research Laboratories.

Mercaptopurine, known chemically as 1,7-dihydro-6H-purine-6-thione monohydrate, is an analogue of the purine bases adenine and hypoxanthine. Its structural formula is:

Mercaptopurine is available in tablet form for oral administration. Each scored tablet contains 50 mg mercaptopurine and the inactive ingredients microcrystalline cellulose NF, lactose monohydrate NF, stearic acid NF, and colloidal silicon dioxide NF.

Mercaptopurine Tablets USP meet USP Dissolution Test 2.

CLINICAL PHARMACOLOGY

Mechanism of Action: Mercaptopurine (6-MP) competes with hypoxanthine and guanine for the enzyme hypoxanthine-guanine phosphoribosyltransferase (HGPRTase) and is itself converted to thioinosinic acid (TIMP). This intracellular nucleotide inhibits several reactions involving inosinic acid (IMP), including the conversion of IMP to xanthylic acid (XMP) and the conversion of IMP to adenylic acid (AMP) via adenylosuccinate (SAMP). In addition, 6-methylthioinosinate (MTIMP) is formed by the methylation of TIMP. Both TIMP and MTIMP have been reported to inhibit glutamine-5-phosphoribosylpyrophosphate amidotransferase, the first enzyme unique to the de novo pathway for purine ribonucleotide synthesis. Experiments indicate that radiolabeled mercaptopurine may be recovered from the DNA in the form of deoxythioguanosine. Some mercaptopurine is converted to nucleotide derivatives of 6-thioguanine (6-TG) by the sequential action of inosinate (IMP) dehydrogenase and xanthylate (XMP) aminase, converting TIMP to thioguanylic acid (TGMP).

Animal tumors that are resistant to mercaptopurine often have lost the ability to convert mercaptopurine to TIMP. However, it is clear that resistance to mercaptopurine may be acquired by other means as well, particularly in human leukemias.

It is not known exactly which of any one or more of the biochemical effects of mercaptopurine and its metabolites are directly or predominantly responsible for cell death.

PHARMACOKINETICS

Pharmacokinetics: Clinical studies have shown that the absorption of an oral dose of mercaptopurine in humans is incomplete and variable, averaging approximately 50% of the administered dose. The factors influencing absorption are unknown. Intravenous administration of an investigational preparation of mercaptopurine revealed a plasma half-disappearance time of 21 minutes in pediatric patients and 47 minutes in adults. The volume of distribution usually exceeded that of the total body water.

Following the oral administration of ^35S-6-mercaptopurine in one subject, a total of 46% of the dose could be accounted for in the urine (as parent drug and metabolites) in the first 24 hours. There is negligible entry of mercaptopurine into cerebrospinal fluid.

Plasma protein binding averages 19% over the concentration range 10 to 50 mcg/mL (a concentration only achieved by intravenous administration of mercaptopurine at doses exceeding 5 to 10 mg/kg).

A reduction in mercaptopurine dosage is required if patients are receiving both mercaptopurine and allopurinol (see PRECAUTIONS and DOSAGE AND ADMINISTRATION).

Metabolism and Genetic Polymorphism: Variability in mercaptopurine metabolism is one of the major causes of interindividual differences in systemic exposure to the drug and its active metabolites. Mercaptopurine activation occurs via hypoxanthine-guanine phosphoribosyl transferase (HGPRT) and several enzymes to form 6-thioguanine nucleotides (6-TGNs). The cytotoxicity of mercaptopurine is due, in part, to the incorporation of 6-TGN into DNA. Mercaptopurine is inactivated via two major pathways. One is thiol methylation, which is catalyzed by the polymorphic enzyme thiopurine S-methyltransferase (TPMT), to form the inactive metabolite methyl-6-MP. TPMT activity is highly variable in patients because of a genetic polymorphism in the TPMT gene. For Caucasians and African Americans, approximately 0.3% (1:300) of patients have two non-functional alleles (homozygous-deficient) of the TPMT gene and have little or no detectable enzyme activity. Approximately 10% of patients have one TPMT non-functional allele (heterozygous) leading to low or intermediate TPMT activity and 90% of individuals have normal TPMT activity with two functional alleles. Homozygous-deficient patients (two non-functional alleles), if given usual doses of mercaptopurine, accumulate excessive cellular concentrations of active thioguanine nucleotides predisposing them to mercaptopurine toxicity (see WARNINGS and PRECAUTIONS). Heterozygous patients with low or intermediate TPMT activity accumulate higher concentrations of active thioguanine nucleotides than people with normal TPMT activity and are more likely to experience mercaptopurine toxicity (see WARNINGS and PRECAUTIONS). TPMT genotyping or phenotyping (red blood cell TPMT activity) can identify patients who are homozygous deficient or have low or intermediate TPMT activity (see WARNINGS, PRECAUTIONS: Laboratory Tests, and DOSAGE AND ADMINISTRATION sections).

Another inactivation pathway is oxidation, which is catalyzed by xanthine oxidase (XO) and forms 6-thiouric acid. Xanthine oxidase is inhibited by ZYLOPRIM® (allopurinol). Concomitant use of allopurinol with mercaptopurine decreases the catabolism of mercaptopurine and its active metabolites leading to mercaptopurine toxicity. A reduction in mercaptopurine dosage is therefore required if patients are receiving both mercaptopurine and allopurinol (see PRECAUTIONS and DOSAGE AND ADMINISTRATION). After oral administration of ^35 S-6-mercaptopurine, urine contains intact mercaptopurine, thiouric acid (formed by direct oxidation by xanthine oxidase, probably via 6-mercapto-8-hydroxypurine), and a number of 6-methylated thiopurines.

INDICATIONS AND USAGE

Mercaptopurine tablets are indicated for maintenance therapy of acute lymphatic (lymphocytic, lymphoblastic) leukemia as part of a combination regimen. The response to this agent depends upon the particular subclassification of acute lymphatic leukemia and the age of the patient (pediatric or adult).

Mercaptopurine is not effective for prophylaxis or treatment of central nervous system leukemia.

Mercaptopurine is not effective in acute myelogenous leukemia, chronic lymphatic leukemia, the lymphomas (including Hodgkins Disease), or solid tumors.

CONTRAINDICATIONS

Mercaptopurine tablets should not be used in patients whose disease has demonstrated prior resistance to this drug. In animals and humans, there is usually complete cross-resistance between mercaptopurine and thioguanine.

Mercaptopurine should not be used in patients who have a hypersensitivity to mercaptopurine or any component of the formulation.

WARNINGS

Mercaptopurine is mutagenic in animals and humans, carcinogenic in animals, and may increase the patient's risk of neoplasia. Cases of hepatosplenic T-cell lymphoma have been reported in patients treated with mercaptopurine for inflammatory bowel disease. The safety and efficacy of mercaptopurine in patients with inflammatory bowel disease have not been established.

Bone Marrow Toxicity: The most consistent, dose-related toxicity is bone marrow suppression. This may be manifest by anemia, leukopenia, thrombocytopenia, or any combination of these. Any of these findings may also reflect progression of the underlying disease. In many patients with severe depression of the formed elements of the blood due to mercaptopurine, the bone marrow appears hypoplastic on aspiration or biopsy, whereas in other cases it may appear normocellular. The qualitative changes in the erythroid elements towards the megaloblastic series, characteristically seen with the folic acid antagonists and some other antimetabolites, are not seen with this drug. Life-threatening infections and bleeding have been observed as a consequence of mercaptopurine-induced granulocytopenia and thrombocytopenia. Since mercaptopurine may have a delayed effect, it is important to withdraw the medication temporarily at the first sign of an unexpected abnormally large fall in any of the formed elements of the blood, if not attributable to another drug or disease process.

Individuals who are homozygous for an inherited defect in the TPMT (thiopurine-S-methyltransferase) gene are unusually sensitive to the myelosuppressive effects of mercaptopurine and prone to developing rapid bone marrow suppression following the initiation of treatment. Laboratory tests are available, both genotypic and phenotypic, to determine the TPMT status. Substantial dose reductions are generally required for homozygous-TPMT deficient patients (two non-functional alleles) to avoid the development of life threatening bone marrow suppression. Although heterozygous patients with intermediate TPMT activity may have increased mercaptopurine toxicity, this is variable, and the majority of patients tolerate normal doses of mercaptopurine. If a patient has clinical or laboratory evidence of severe toxicity, particularly myelosuppression, TPMT testing should be considered. In patients who exhibit excessive myelosuppression due to 6-mercaptopurine, it may be possible to adjust the mercaptopurine dose and administer the usual dosage of other myelosuppressive chemotherapy as required for treatment (see DOSAGE AND ADMINISTRATION).

Bone marrow toxicity may be more profound in patients treated with concomitant allopurinol (see PRECAUTIONS: Drug Interactions and DOSAGE AND ADMINISTRATION). This problem could be exacerbated by coadministration with drugs that inhibit TPMT, such as olsalazine, mesalazine, or sulphasalazine.

Hepatotoxicity: Mercaptopurine is hepatotoxic in animals and humans. A small number of deaths have been reported that may have been attributed to hepatic necrosis due to administration of mercaptopurine. Hepatic injury can occur with any dosage, but seems to occur with more frequency when doses of 2.5 mg/kg/day are exceeded. The histologic pattern of mercaptopurine hepatotoxicity includes features of both intrahepatic cholestasis and parenchymal cell necrosis, either of which may predominate. It is not clear how much of the hepatic damage is due to direct toxicity from the drug and how much may be due to a hypersensitivity reaction. In some patients jaundice has cleared following withdrawal of mercaptopurine and reappeared with its reintroduction.

Published reports have cited widely varying incidences of overt hepatotoxicity. In a large series of patients with various neoplastic diseases, mercaptopurine was administered orally in doses ranging from 2.5 mg/kg to 5.0 mg/kg without evidence of hepatotoxicity. It was noted by the authors that no definite clinical evidence of liver damage could be ascribed to the drug, although an occasional case of serum hepatitis did occur in patients receiving 6-MP who previously had transfusions. In reports of smaller cohorts of adult and pediatric leukemic patients, the incidence of hepatotoxicity ranged from 0% to 6%. In an isolated report by Einhorn and Davidsohn, jaundice was observed more frequently (40%), especially when doses exceeded 2.5 mg/kg. Usually, clinically detectable jaundice appears early in the course of treatment (1 to 2 months). However, jaundice has been reported as early as 1 week and as late as 8 years after the start of treatment with mercaptopurine. The hepatotoxicity has been associated in some cases with anorexia, diarrhea, jaundice and ascites. Hepatic encephalopathy has occurred.

Monitoring of serum transaminase levels, alkaline phosphatase, and bilirubin levels may allow early detection of hepatotoxicity. It is advisable to monitor these liver function tests at weekly intervals when first beginning therapy and at monthly intervals thereafter. Liver function tests may be advisable more frequently in patients who are receiving mercaptopurine with other hepatotoxic drugs or with known pre-existing liver disease. The onset of clinical jaundice, hepatomegaly, or anorexia with tenderness in the right hypochondrium are immediate indications for withholding mercaptopurine until the exact etiology can be identified. Likewise, any evidence of deterioration in liver function studies, toxic hepatitis, or biliary stasis should prompt discontinuation of the drug and a search for an etiology of the hepatotoxicity.

The concomitant administration of mercaptopurine with other hepatotoxic agents requires especially careful clinical and biochemical monitoring of hepatic function. Combination therapy involving mercaptopurine with other drugs not felt to be hepatotoxic should nevertheless be approached with caution. The combination of mercaptopurine with doxorubicin was reported to be hepatotoxic in 19 of 20 patients undergoing remission-induction therapy for leukemia resistant to previous therapy.

Immunosuppression: Mercaptopurine recipients may manifest decreased cellular hypersensitivities and decreased allograft rejection. Induction of immunity to infectious agents or vaccines will be subnormal in these patients; the degree of immunosuppression will depend on antigen dose and temporal relationship to drug. This immunosuppressive effect should be carefully considered with regard to intercurrent infections and risk of subsequent neoplasia.

Pregnancy: Pregnancy Category D. Mercaptopurine can cause fetal harm when administered to a pregnant woman. Women receiving mercaptopurine in the first trimester of pregnancy have an increased incidence of abortion; the risk of malformation in offspring surviving first trimester exposure is not accurately known. In a series of 28 women receiving mercaptopurine after the first trimester of pregnancy, 3 mothers died undelivered, 1 delivered a stillborn child, and 1 aborted; there were no cases of macroscopically abnormal fetuses. Since such experience cannot exclude the possibility of fetal damage, mercaptopurine should be used during pregnancy only if the benefit clearly justifies the possible risk to the fetus, and particular caution should be given to the use of mercaptopurine in the first trimester of pregnancy.

There are no adequate and well-controlled studies in pregnant women. If this drug is used during pregnancy or if the patient becomes pregnant while taking the drug, the patient should be apprised of the potential hazard to the fetus. Women of childbearing potential should be advised to avoid becoming pregnant.

PRECAUTIONS

GENERAL PRECAUTIONS

General: The safe and effective use of mercaptopurine demands close monitoring of the CBC and patient clinical status. After selection of an initial dosage schedule, therapy will frequently need to be modified depending upon the patient's response and manifestations of toxicity. It is probably advisable to start with lower dosages in patients with impaired renal function, due to slower elimination of the drug and metabolites and a greater cumulative effects.

PATIENT COUNSELING INFORMATION

Information for Patients: Patients should be informed that the major toxicities of mercaptopurine are related to myelosuppression, hepatotoxicity, and gastrointestinal toxicity. Patients should never be allowed to take the drug without medical supervision and should be advised to consult their physician if they experience fever, sore throat, jaundice, nausea, vomiting, signs of local infection, bleeding from any site, or symptoms suggestive of anemia. Women of childbearing potential should be advised to avoid becoming pregnant.

LABORATORY TESTS

Laboratory Tests: (Also see WARNINGS, Bone Marrow Toxicity) It is recommended that evaluation of the hemoglobin or hematocrit, total white blood cell count and differential count, and quantitative platelet count be obtained weekly while the patient is on therapy with mercaptopurine. Bone marrow examination may also be useful for the evaluation of marrow status. The decision to increase, decrease, continue, or discontinue a given dosage of mercaptopurine must be based upon the degree of severity and rapidity with which changes are occurring. In many instances, particularly during the induction phase of acute leukemia, complete blood counts will need to be done more frequently than once weekly in order to evaluate the effect of the therapy. If a patient has clinical or laboratory evidence of severe bone marrow toxicity, particularly myelosuppression, TPMT testing should be considered.

TPMT Testing: Genotypic and phenotypic testing of TPMT status are available. Genotypic testing can determine the allelic pattern of a patient. Currently, 3 alleles—TPMT*2, TPMT*3A and TPMT*3C—account for about 95% of individuals with reduced levels of TPMT activity. Individuals homozygous for these alleles are TPMT deficient and those heterozygous for these alleles have variable TPMT (low or intermediate) activity. Phenotypic testing determines the level of thiopurine nucleotides or TPMT activity in erythrocytes and can also be informative. Caution must be used with phenotyping since some co-administered drugs can influence measurement of TPMT activity in blood, and recent blood transfusions will misrepresent a patient's actual TPMT activity.

DRUG INTERACTIONS

Drug Interactions: When allopurinol and mercaptopurine are administered concomitantly, the dose of mercaptopurine must be reduced to one third to one quarter of the usual dose to avoid severe toxicity.

There is usually complete cross-resistance between mercaptopurine and thioguanine.

The dosage of mercaptopurine may need to be reduced when this agent is combined with other drugs whose primary or secondary toxicity is myelosuppression. Enhanced marrow suppression has been noted in some patients also receiving trimethoprim-sulfamethoxazole.

Inhibition of the anticoagulant effect of warfarin, when given with mercaptopurine, has been reported.

As there is in vitro evidence that aminosalicylate derivatives (e.g., olsalazine, mesalazine, or sulphasalazine) inhibit the TPMT enzyme, they should be administered with caution to patients receiving concurrent mercaptopurine therapy (see WARNINGS).

CARCINOGENESIS AND MUTAGENESIS AND IMPAIRMENT OF FERTILITY

Carcinogenesis, Mutagenesis, Impairment of Fertility: Mercaptopurine causes chromosomal aberrations in animals and humans and induces dominant-lethal mutations in male mice. In mice, surviving female offspring of mothers who received chronic low doses of mercaptopurine during pregnancy were found sterile, or if they became pregnant, had smaller litters and more dead fetuses as compared to control animals. Carcinogenic potential exists in humans, but the extent of the risk is unknown.

The effect of mercaptopurine on human fertility is unknown for either males or females.

PREGNANCY

Pregnancy: Teratogenic Effects: Pregnancy Category D. See WARNINGS section.

NURSING MOTHERS

Nursing Mothers: It is not known whether this drug is excreted in human milk. Because many drugs are excreted in human milk, and because of the potential for serious adverse reactions in nursing infants from mercaptopurine, a decision should be made whether to discontinue nursing or to discontinue the drug, taking into account the importance of the drug to the mother.

Pediatric Use: See DOSAGE AND ADMINISTRATION section.

GERIATRIC USE

Geriatric Use: Clinical studies of mercaptopurine therapy did not include sufficient numbers of subjects aged 65 and over to determine whether they respond differently from younger subjects. Other reported clinical experience has not identified differences in responses between the elderly and younger patients. In general, dose selection for an elderly patient should be cautious, usually starting at the low end of the dosing range, reflecting the greater frequency of decreased hepatic, renal, or cardiac function, and of concomitant disease or other drug therapy.

ADVERSE REACTIONS

The principal and potentially serious toxic effects of mercaptopurine are bone marrow toxicity and hepatotoxicity (see WARNINGS and PRECAUTIONS).

Hematologic: The most frequent adverse reaction to mercaptopurine is myelosuppression. The induction of complete remission of acute lymphatic leukemia frequently is associated with marrow hypoplasia. Patients without TPMT enzyme activity (homozygous-deficient) are particularly susceptible to hematologic toxicity, and some patients with low or intermediate TPMT enzyme activity are more susceptible to hematologic toxicity than patients with normal TPMT activity (see WARNINGS: Bone Marrrow Toxicity), although the latter can also experience severe toxicity. Maintenance of remission generally involves multiple-drug regimens whose component agents cause myelosuppression. Anemia, leukopenia, and thrombocytopenia are frequently observed. Dosages and also schedules are adjusted to prevent life-threatening cytopenias.

Renal: Hyperuricemia and/or hyperuricosuria may occur in patients receiving mercaptopurine as a consequence of rapid cell lysis accompanying the antineoplastic effect. Renal adverse effects can be minimized by increased hydration, urine alkalinization, and the prophylactic administration of a xanthine oxidase inhibitor such as allopurinol. The dosage of mercaptopurine should be reduced to one third to one quarter of the usual dose if allopurinol is given concurrently.

Gastrointestinal: Intestinal ulceration has been reported. Nausea, vomiting, and anorexia are uncommon during initial administration, but may increase with continued administration. Mild diarrhea and sprue-like symptoms have been noted occasionally, but it is difficult at present to attribute these to the medication. Oral lesions are rarely seen, and when they occur they resemble thrush rather than antifolic ulcerations.

Miscellaneous: The administration of mercaptopurine has been associated with skin rashes and hyperpigmentation. Alopecia has been reported.

Drug fever has been very rarely reported with mercaptopurine. Before attributing fever to mercaptopurine, every attempt should be made to exclude more common causes of pyrexia, such as sepsis, in patients with acute leukemia. Oligospermia has been reported.

OVERDOSAGE

Signs and symptoms of overdosage may be immediate (anorexia, nausea, vomiting and diarrhea); or delayed (myelosuppression, liver dysfunction, and gastroenteritis). Dialysis cannot be expected to clear mercaptopurine. Hemodialysis is thought to be of marginal use due to the rapid intracellular incorporation of mercaptopurine into active metabolites with long persistence. The oral LD50 of mercaptopurine was determined to be 480 mg/kg in the mouse and 425 mg/kg in the rat.

There is no known pharmacologic antagonist of mercaptopurine. The drug should be discontinued immediately if unintended toxicity occurs during treatment. If a patient is seen immediately following an accidental overdosage of the drug, it may be useful to induce emesis.

DOSAGE AND ADMINISTRATION

Maintenance Therapy: Once a complete hematologic remission is obtained, maintenance therapy is considered essential. Maintenance doses will vary from patient to patient. The usual daily maintenance dose of mercaptopurine is 1.5 to 2.5 mg/kg/day as a single dose. It is to be emphasized that in pediatric patients with acute lymphatic leukemia in remission, superior results have been obtained when mercaptopurine has been combined with other agents (most frequently with methotrexate) for remission maintenance. Mercaptopurine should rarely be relied upon as a single agent for the maintenance of remissions induced in acute leukemia.

Procedures for proper handling and disposal of anticancer drugs should be considered. Several guidelines on this subject have been published. ^1-8

There is no general agreement that all of the procedures recommended in the guidelines are necessary or appropriate.

Dosage with Concomitant Allopurinol: When allopurinol and mercaptopurine are administered concomitantly, the dose of mercaptopurine must be reduced to one third to one quarter of the usual dose to avoid severe toxicity.

Dosage in TPMT-deficient Patients: Patients with inherited little or no thiopurine-S-methyltransferase (TPMT) activity are at increased risk for severe mercaptopurine toxicity from conventional doses of mercaptopurine and generally require substantial dose reduction. The optimal starting dose for homozygous deficient patients has not been established (see CLINICAL PHARMACOLOGY, WARNINGS and PRECAUTIONS sections).

Most patients with heterozygous TPMT deficiency tolerated recommended mercaptopurine doses, but some require dose reduction. Genotypic and phenotypic testing of TPMT status are available. (See CLINICAL PHARMACOLOGY, WARNINGS, and PRECAUTIONS sections.)

Dosage in Renal and Hepatic Impairment: It is probably advisable to start with lower dosages in patients with impaired renal function, due to slower elimination of the drug and metabolites and a greater cumulative effect. Consideration should be given to reducing the dosage in patients with impaired hepatic function.

HOW SUPPLIED

Light yellow to off white, diamond shaped, scored tablets containing 50 mg mercaptopurine, debossed with “P02”;

Bottles of 30 | NDC 54868-5282-2
Bottles of 60 | NDC 54868-5282-0

Store at 20° to 25°C (68°to 77°F) in a dry place. See USP controlled room temperature.

REFERENCES

1. ONS Clinical Practice Committee. Cancer Chemotherapy Guidelines and Recommendations for Practice. Pittsburgh, PA: Oncology Nursing Society; 1999:32-41.
2. Recommendations for the safe handling of parenteral antineoplastic drugs. Washington, DC: Division of Safety; Clinical Center Pharmacy Department and Cancer Nursing Services, National Institutes of Health; 1992. US Dept of Health and Human Services. Public Health Service publication NIH 92-2621.
3. AMA Council on Scientific Affairs. Guidelines for handling parenteral antineoplastics. JAMA. 1985; 253:1590-1591.
4. National Study Commission on Cytotoxic Exposure. Recommendations for handling cytotoxic agents. 1987. Available from Louis P. Jeffrey, Chairman, National Study Commission on Cytotoxic Exposure. Massachusetts College of Pharmacy and Allied Health Sciences, 179 Longwood Avenue, Boston, MA 02115.
5. Clinical Oncological Society of Australia. Guidelines and recommendations for safe handling of antineoplastic agents. Med J Australia. 1983; 1:426-428.
6. Jones RB, Frank R, Mass T. Safe handling of chemotherapeutic agents: a report from the Mount Sinai Medical Center. CA-A Cancer J for Clinicians. 1983;33:258-263.
7. American Society of Hospital Pharmacists. ASHP technical assistance bulletin on handling cytotoxic and hazardous drugs. Am J Hosp Pharm. 1990;47:1033-1049.
8. Controlling Occupational Exposure to Hazardous Drugs. (OSHA Work-Practice Guidelines.) Am J Health-Syst Pharm. 1996;53:1669-1685.

Distributed by:
PAR PHARMACEUTICAL COMPANIES, INC.
Spring Valley, NY 10977

ZYLOPRIM® is a registered trademark of Prometheus Laboratories Inc.

Revised: 05/12
OS922-02-1-06
MR001C

Distributed and Repackaged by:
Physicians Total Care, Inc.
Tulsa, Oklahoma 74146

Principal Display Panel

50mg

Mercaptopurine Tablets,
USP
Rx only
Cytotoxic agent